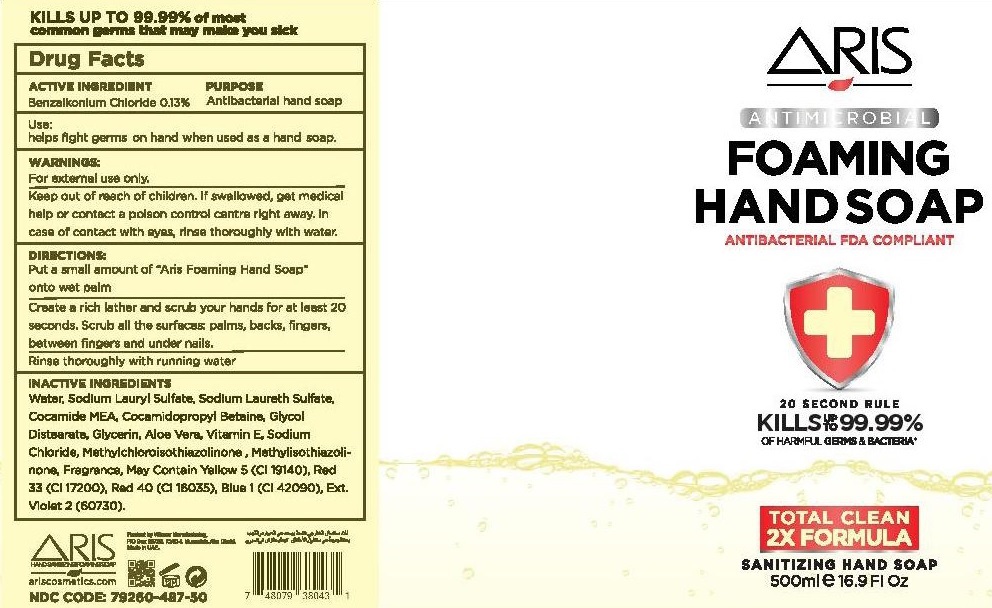 DRUG LABEL: Aris Foaming HandSoap
NDC: 79260-487 | Form: LIQUID
Manufacturer: WINNER MANUFACTURING
Category: otc | Type: HUMAN OTC DRUG LABEL
Date: 20200710

ACTIVE INGREDIENTS: BENZALKONIUM CHLORIDE 0.13 g/100 mL
INACTIVE INGREDIENTS: WATER; SODIUM LAURYL SULFATE; SODIUM LAURETH-3 SULFATE; COCO MONOETHANOLAMIDE; COCAMIDOPROPYL BETAINE; GLYCOL DISTEARATE; GLYCERIN; ALOE VERA LEAF; .ALPHA.-TOCOPHEROL; SODIUM CHLORIDE; METHYLCHLOROISOTHIAZOLINONE; METHYLISOTHIAZOLINONE; FD&C YELLOW NO. 5; D&C RED NO. 33; FD&C RED NO. 40; FD&C BLUE NO. 1; EXT. D&C VIOLET NO. 2

ARIS FOAMING HAND SOAP

ACTIVE INGREDIENT

Benzalkonium Chloride 0.13%

PURPOSE

Antibacterial hand soap

Use:

helps fight germs on hand when used as a hand soap.

WARNINGS:

For external use only.

Keep out of reach of children. If swallowed, get medical help or contact a poison control centre right away. In case of contact with eyes, rinse thoroughly with water.

DIRECTIONS:

Put a small amount of "Aris Foaming Hand Soap" onto wet palm

Create a rich lather and scrub your hands for at least 20 seconds. Scrub all the surfaces, palms, backs, fingers, between fingers and under nails.

Rinse thoroughly with running water

INACTIVE INGREDIENTS

Water, Sodium Lauryl Sulphate, Sodium Laureth Sulfate, Cocamide MEA, Cocamidopropyl Betaine, Glycol Distearate, Glycerin, Aloe Vera, Vitamin E, Sodium Chloride, Methylchloroisothiazolinone, Methylisothiazolinone, Fragrance, May Contain Yellow 5 (CI 19140), Red 33 (CI 17200), Red 40 (CI 18035), Blue 1 (42090), Ext.Violet 2 (60730).

ANTIMICROBIAL

ANTIBACTERIAL FDA COMPLIANT

20 SECOND RULE

KILLS UP TO 99.99% OF HARMFUL GERMS & BACTERIA*

TOTAL CLEAN

2X FORMULA

SANITIZING HAND SOAP

KILLS UP TO 99.99% of most common germs that may make you sick

ariscosmetics.com

Produced by Winner Manufacturing

Made in UAE